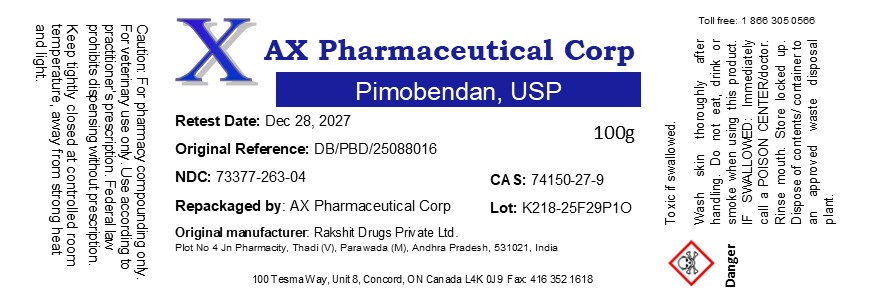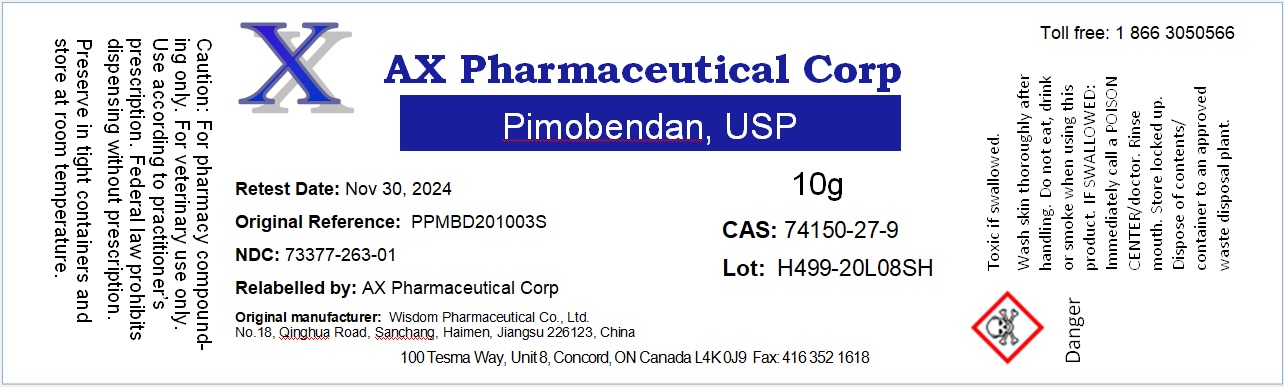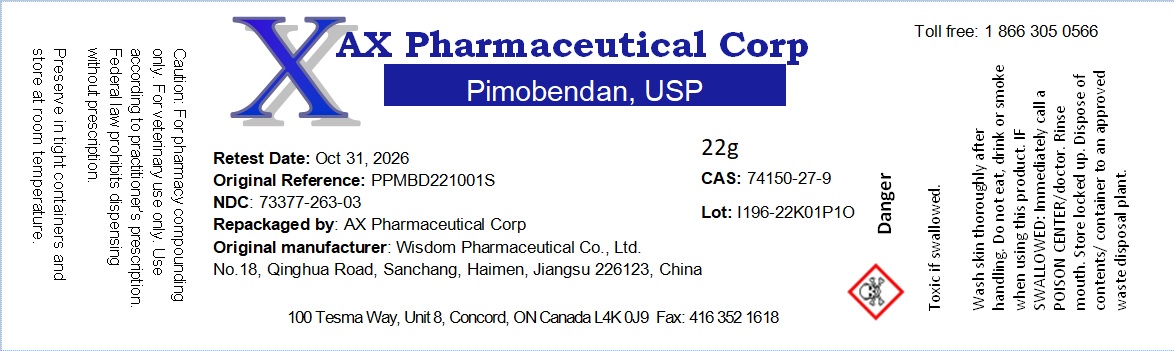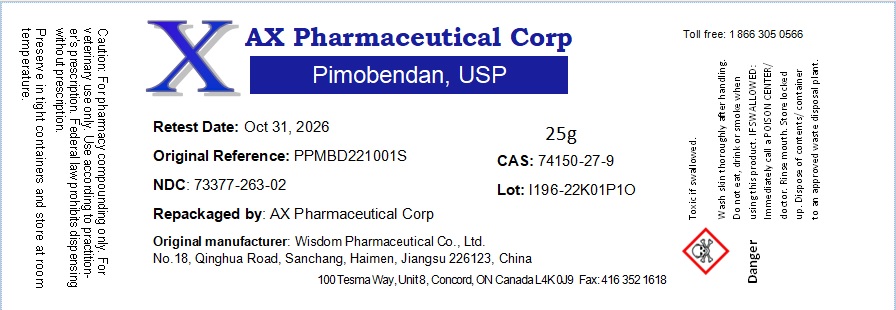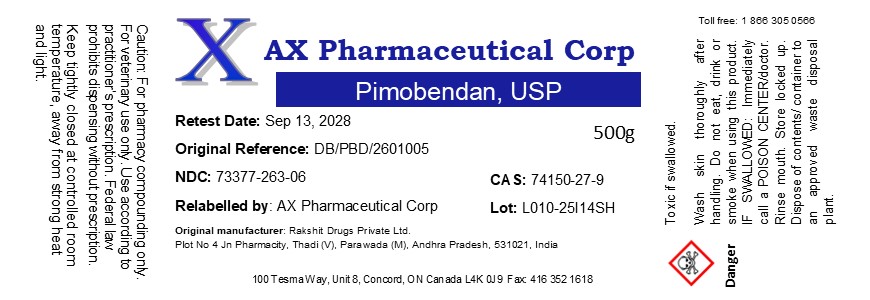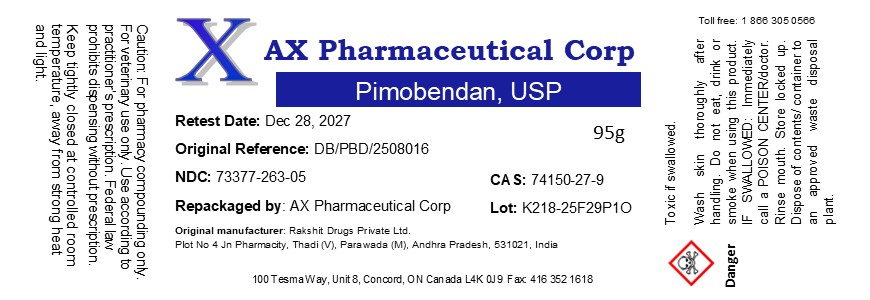 DRUG LABEL: Pimobendan
NDC: 73377-263 | Form: POWDER
Manufacturer: AX Pharmaceutical Corp
Category: other | Type: BULK INGREDIENT - ANIMAL DRUG
Date: 20260226

ACTIVE INGREDIENTS: PIMOBENDAN 1 g/1 g

Pimobendan